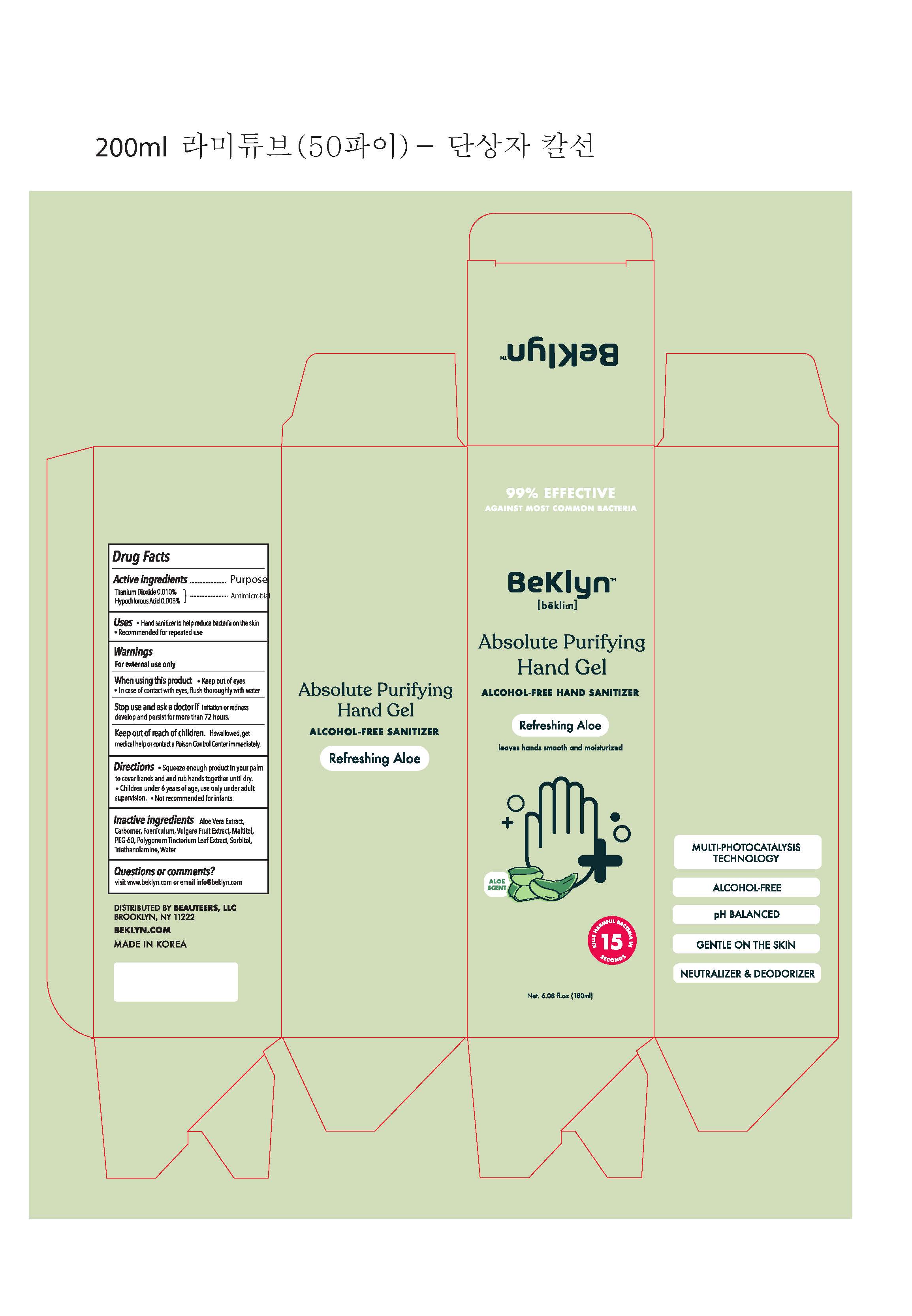 DRUG LABEL: Beklyn Absolute Purifying Hand Gel Refreshing Aloe 180ml
NDC: 71544-0018 | Form: GEL
Manufacturer: MY Corp.,Ltd
Category: otc | Type: HUMAN OTC DRUG LABEL
Date: 20200904

ACTIVE INGREDIENTS: TITANIUM DIOXIDE 0.018 g/180 mL; HYPOCHLOROUS ACID 0.0144 g/180 mL
INACTIVE INGREDIENTS: ALOE VERA LEAF; CARBOMER HOMOPOLYMER, UNSPECIFIED TYPE; MALTITOL; POLYETHYLENE GLYCOL 3000; PERSICARIA TINCTORIA LEAF; SORBITOL; TROLAMINE; WATER

MY Corp - Beklyn Absolute Purifying Hand Gel

ACTIVE INGREDIENT

titanium dioxide, hypochlorous acid

INACTIVE INGREDIENT

Aloe Vera Extract, Carbomer, Foeniculum Vulgare Fruit Extract, Maltitol, PEG-60, Polygonum Tinctorium Leaf Extract, Sorbitol, Triethanolamine, Water

PURPOSE

Hand sanitizer to help reduce bacteria that potentially can cause disease. Recommended for repeated use

keep out of reach of the children

INDICATIONS AND USAGE

- Squeeze enough product in your palm to cover hands and rub hands together until dry.
- For children under 6 years use adult supervision
- Not recommended for infants

WARNINGS

For external use only.

When using this product keep out of eyes, ears, and mouth. In case of contact with eyes, rinse thoroughly with water.

Stop use and ask a doctor if irritation or rash occurs develop and persist for more than 72 hours.

Keep out of reach of children. If swallowed, get medical help or contact a Poison Control Center right away.

DOSAGE AND ADMINISTRATION

for external use only